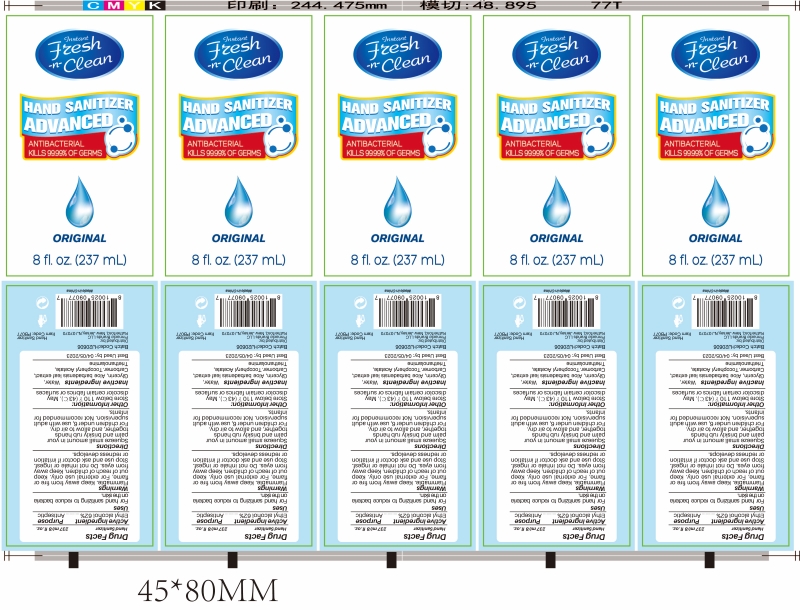 DRUG LABEL: Hand Sanitizer Gel
NDC: 73788-101 | Form: GEL
Manufacturer: Hangzhou Huiji Biotechnology Co., Ltd.
Category: otc | Type: HUMAN OTC DRUG LABEL
Date: 20220224

ACTIVE INGREDIENTS: ALCOHOL 62 mL/100 mL
INACTIVE INGREDIENTS: WATER; GLYCERIN; ALOE VERA LEAF; TROLAMINE; CARBOMER 934; .ALPHA.-TOCOPHEROL ACETATE

73788-101 Hand Sanitizer Gel

Active Ingredient

Ethyl Alcohol 62%

Purpose

Antiseptic

Use

For hand sanitizing to reduce bacteria
on the skin.

WARNINGS

Flammable. Keep away from fire or
flame. For external use only. Keep
out of reach of children. Keep away
from eyes. Do not inhale or ingest.
Stop use and ask doctor if irritation
or redness develops.

keep out of reach of children

Directions

Squeeze small amount in your
palm and briskly rub hands
together, and allow to air dry.
For children under 6, use with adult
supervision. Not recommended for
infants.

Other Information

Store below 110 F (43 C). May
discolor certain fabrics or surfaces

Inactive ingredients

Inactive ingredients Water,
Glycerin, Aloe barbadensis leaf extract,
Carbomer.Tocopheryl Acetate,
Triethanolamine